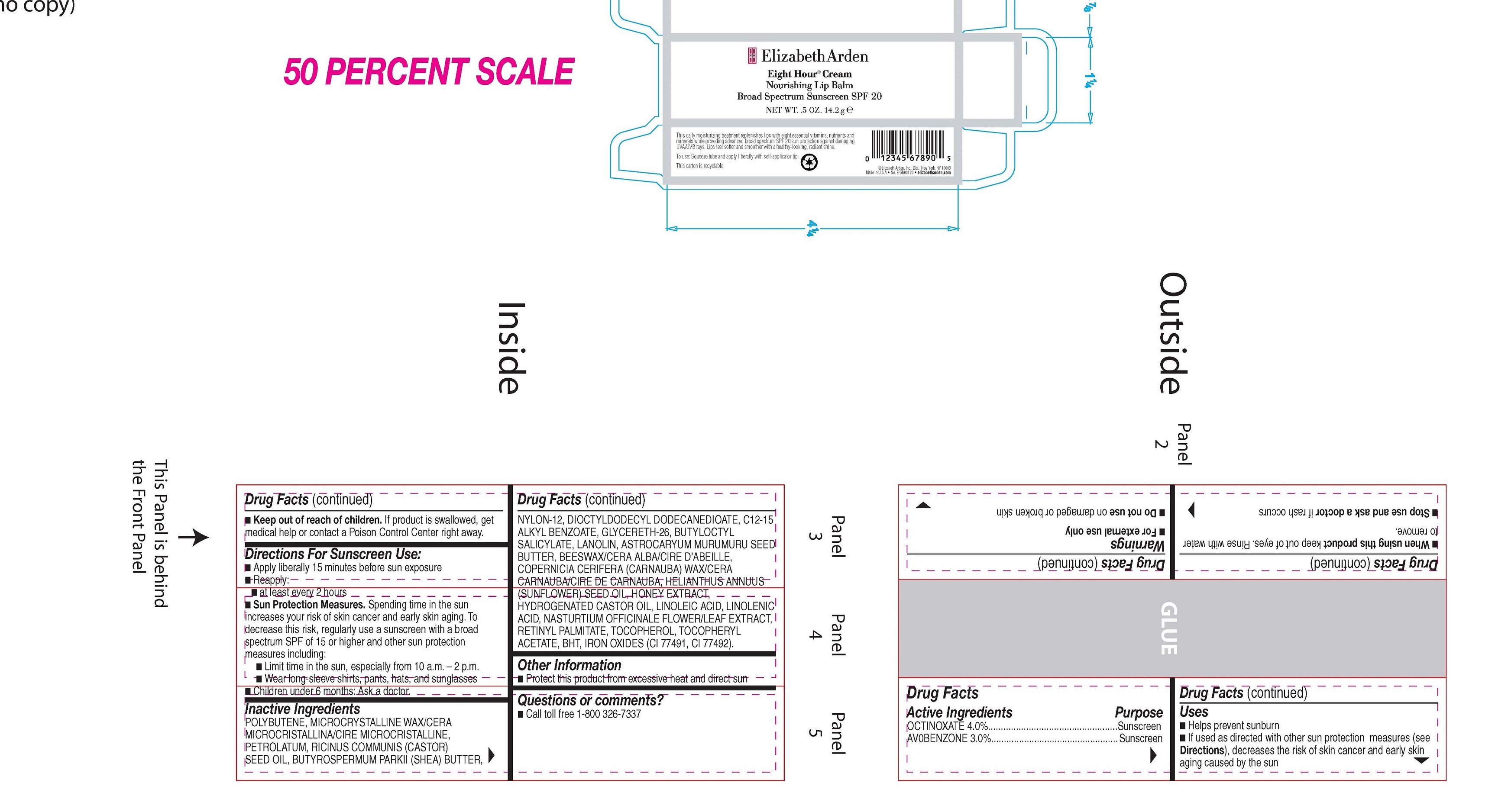 DRUG LABEL: EIGHT HOUR NOURISHING LIP SPF 20
NDC: 10967-671 | Form: EMULSION
Manufacturer: REVLON
Category: otc | Type: HUMAN OTC DRUG LABEL
Date: 20251229

ACTIVE INGREDIENTS: OCTINOXATE 4 mg/1 g; AVOBENZONE 3 mg/1 g
INACTIVE INGREDIENTS: POLYBUTENE (1400 MW); CASTOR OIL; NYLON-12; SUNFLOWER OIL; BUTYLATED HYDROXYTOLUENE; FERRIC OXIDE RED; VITAMIN A PALMITATE; .ALPHA.-TOCOPHEROL ACETATE; ASTROCARYUM MURUMURU SEED BUTTER; HYDROGENATED CASTOR OIL; LANOLIN; MICROCRYSTALLINE WAX; SHEA BUTTER; GLYCERETH-26; FERRIC OXIDE YELLOW; LINOLEIC ACID; ALKYL (C12-15) BENZOATE; YELLOW WAX; HONEY; LINOLENIC ACID; TOCOPHEROL; BUTYLOCTYL SALICYLATE; PETROLATUM; DIOCTYLDODECYL DODECANEDIOATE

ELIZABETH ARDEN EIGHT HOUR CREAM NOURISHING LIP BALM BROAD SPECTRUM SUNSCREEN SPF 20

Active Ingredients

Active Ingredients Purpose
OCTINOXATE 4.0%...................................................Sunscreen
AV0BENZONE 3.0%..................................................Sunscreen

Inactive Ingredients

POLYBUTENE, MICROCRYSTALLINE WAX/CERA MICROCRISTALLINA/CIRE MICROCRISTALLINE, PETROLATUM, RICINUS COMMUNIS (CASTOR) SEED OIL, BUTYROSPERMUM PARKII (SHEA) BUTTER, NYLON-12, DIOCTYLDODECYL DODECANEDIOATE, C12-15 ALKYL BENZOATE, GLYCERETH-26, BUTYLOCTYL SALICYLATE, LANOLIN, ASTROCARYUM MURUMURU SEED BUTTER, BEESWAX/CERA ALBA/CIRE D'ABEILLE, COPERNICIA CERIFERA (CARNAUBA) WAX/CERA CARNAUBA/CIRE DE CARNAUBA, HELIANTHUS ANNUUS (SUNFLOWER) SEED OIL, HONEY EXTRACT, HYDROGENATED CASTOR OIL, LINOLEIC ACID, LINOLENIC ACI, NASTURTIUM OFFICINALE FLOWER/LEAF EXTRACT, RETINYL PALMITATE, TO DCOPHEROL, TOCOPHERYL ACETATE, BHT, IRON OXIDES (CI 77491, CI 77492).

Uses

- Helps prevent sunburn

- If used as directed with other sun protection measures (see Directions), decreases the risk of skin cancer and early skin aging caused by the sun

Warnings

- For external use only

- Do not use on damaged or broken skin

- When using this product keep out of eyes. Rinse with water to remove.
- Stop use and ask a doctor if rash occurs

- Keep out of reach of children. If product is swallowed, get medical help or contact a Poison Control Center right away.

Directions For Sunscreen Use

- Apply liberally 15 minutes before sun exposure
- Reapply:

- at least every 2 hours
- Sun Protection Measures. Spending time in the sun increases your risk of skin cancer and early skin aging. To decrease this risk, regularly use a sunscreen with a broad spectrum SPF of 15 or higher and other sun protection measures including:
- Limit time in the sun, especially from 10 a.m. – 2 p.m.
- Wear long-sleeve shirts, pants, hats, and sunglasses

- Children under 6 months: Ask a doctor.

DOSAGE AND ADMINISTRATION

- Apply liberally 15 minutes before sun exposure
- Reapply at least every 2 hours

INDICATIONS AND USAGE

- Helps prevent sunburn
- If used as directed with other sun protection measures (see Directions), decreases the risk of skin cancer and early skin againg caused by the sun

Keep Out of Reach of Children. If product is swallowed, get medical help or contact a poison control center right away.

PURPOSE

Sunscreen

WARNINGS

- For external use only.
- Do not use on damaged or broken skin.
- When using this product keep out of eyes. Rinse with water to remove.
- Stop using and ask a doctor if rash occurs.